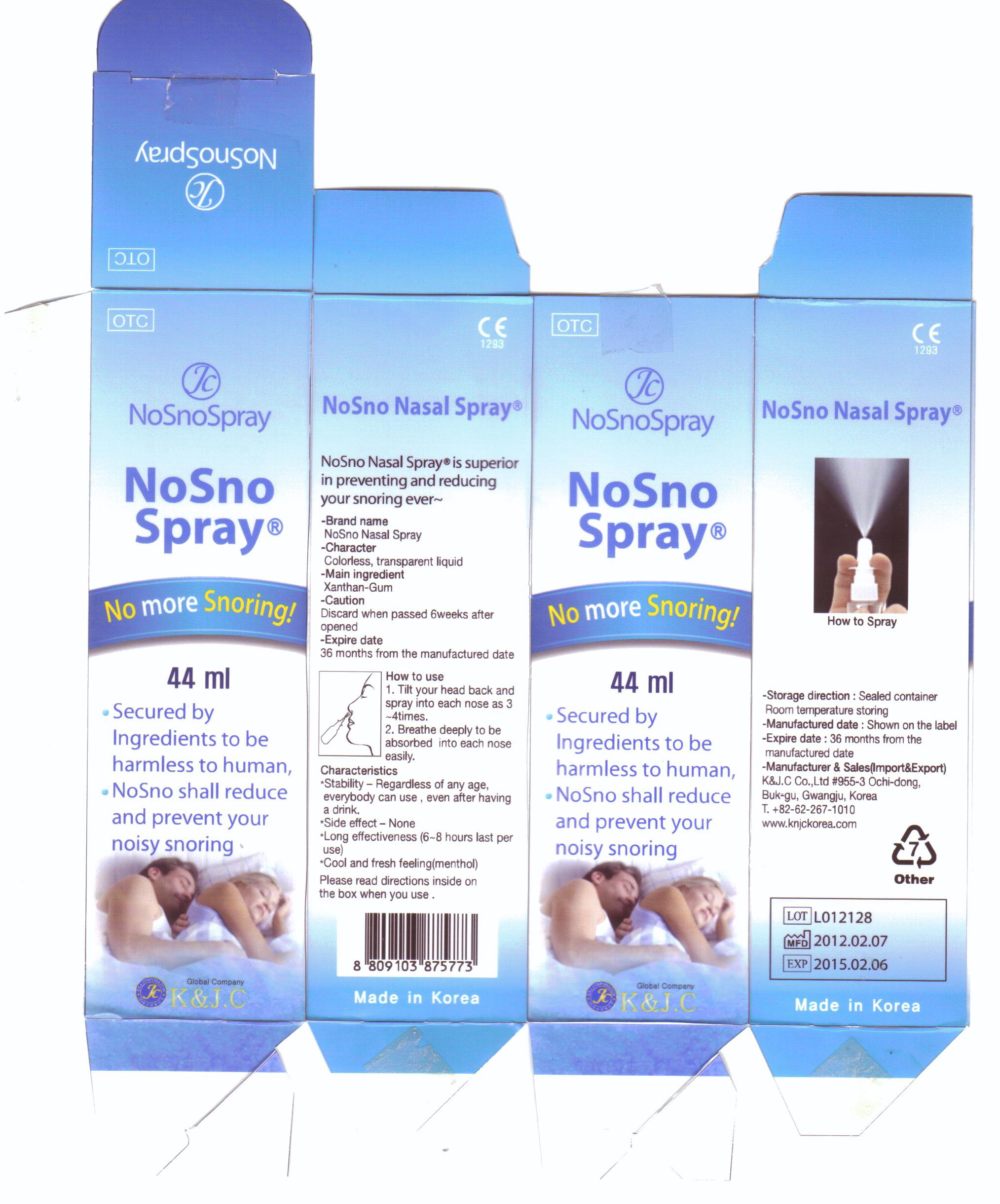 DRUG LABEL: NoSno
NDC: 52345-5001 | Form: LIQUID
Manufacturer: K&J.C Co., Ltd
Category: otc | Type: HUMAN OTC DRUG LABEL
Date: 20120303

ACTIVE INGREDIENTS: XANTHAN GUM 0.05 mL/44 mL
INACTIVE INGREDIENTS: HYALURONATE SODIUM; PROPOLIS WAX; POLYSORBATE 80; LEVOMENTHOL; METHYLPARABEN; WATER

Drug Facts

active ingredient: xanthan gum

inactive ingredient: sodium hyaluronate, propolis, polysorbate, L-menthol, methyl p-hydroxybenzoate, purified water

PURPOSE

reduce and prevent noisy snoring

keep out of reach of the children

INDICATIONS AND USAGE

tilt your head back and spray into each nose as 3~4 times
breathe deeply to be absorbed into each nose easily

WARNINGS

discard when passed 6 weeks after open

DOSAGE AND ADMINISTRATION

nasal use only